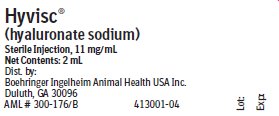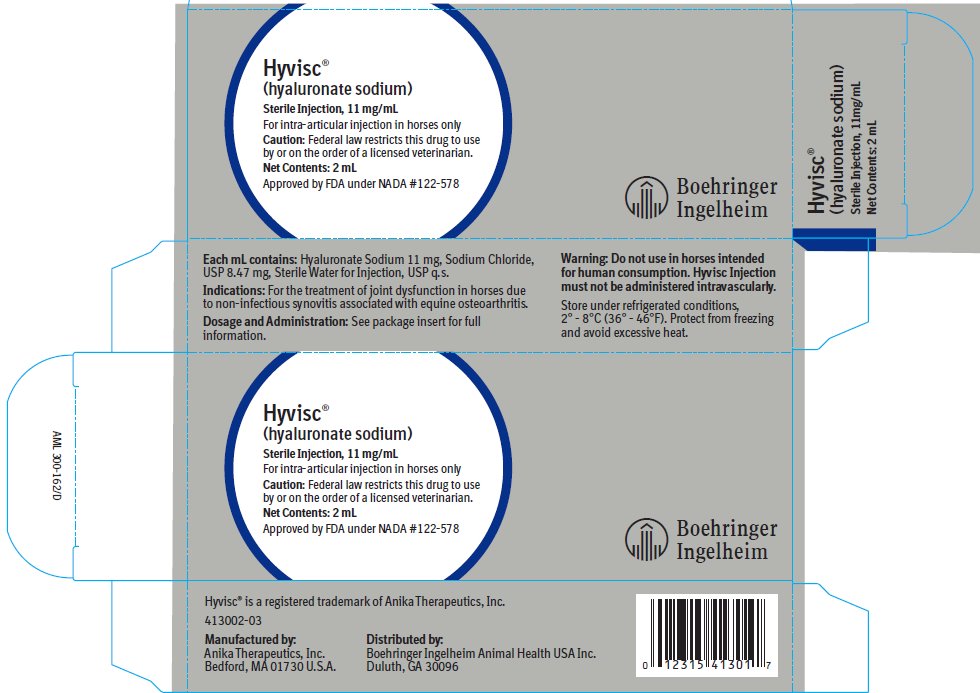 DRUG LABEL: Hyvisc
NDC: 0010-4130 | Form: INJECTION
Manufacturer: Boehringer Ingelheim Animal Health USA Inc.
Category: animal | Type: PRESCRIPTION ANIMAL DRUG LABEL
Date: 20220426

ACTIVE INGREDIENTS: HYALURONATE SODIUM 11 mg/1 mL
INACTIVE INGREDIENTS: WATER

Hyvisc®
(hyaluronate sodium)
Sterile Injection, 11 mg/mL

For intra-articular injection in horses only

Caution:

Federal law restricts this drug to use by or on the order of a licensed veterinarian.

Description:

Hyvisc® (hyaluronate sodium) Injection is a clear, colorless, viscous fluid contained in a 5 mL disposable syringe, as a single 2 mL dose. Chemically, hyaluronic acid is a high molecular weight mucopolysaccharide composed of repeating disaccharide units, each unit consisting of D-glucuronic acid and N-acetyl-D-glucosamine. Each mL of Hyvisc Injection contains 11 mg of hyaluronate sodium and 8.47 mg of sodium chloride, USP, in sterile water for injection, USP, q.s.

Actions:

Hyaluronate sodium is a natural constituent of connective tissue and synovial fluid in both man and animals. In synovial fluid, hyaluronate sodium confers viscoelastic as well as lubricating properties^1,2. In connective tissue, hyaluronate sodium specifically interacts with cartilage proteoglycans to form stable aggregates^3,4,5. The mechanism of action by which exogenous hyaluronate sodium exerts its therapeutic effect in arthritic joints is not known at this time.

Indications:

Hyvisc (hyaluronate sodium) Injection is recommended for the treatment of joint dysfunction in horses due to non-infectious synovitis associated with equine osteoarthritis.

Dosage and Administration:

The recommended dose of Hyvisc (hyaluronate sodium) Injection is 2 mL (22 mg) given to horses intra-articularly in small and medium-sized joints (carpal, fetlock). In larger joints (hock), the dosage is 4 mL (44 mg). Treatment may be repeated at weekly intervals for a total of three treatments. As with any intra-articular injection, aseptic technique is used. The following are suggested use directions regardless of the type of joint to be treated.

1. Carefully diagnose each case using routine methods. The origin of lameness should be pinpointed to be within a specific joint or joints (e.g., lameness is localized to a specific joint using intra-articular anesthesia). Radiographs or other diagnostic aids should not reveal recent fractures or other serious abnormalities which would suggest a poor prognosis.
2. Aseptically remove as much synovial fluid from the afflicted joint as can be easily withdrawn.
3. Remove tip cap from the Hyvisc syringe and inject through a sterile needle, 20 gauge or larger.
4. Inject a single 2 mL dose (one syringe) of Hyvisc into each joint to be treated; if the joint being treated is the hock joint, inject 4 mL (two syringes). Since Hyvisc is a viscous fluid, care should be exercised on injection so as not to dislodge the needle from the syringe.
5. Two or four days of rest or light exercise is recommended before resumption of normal activity. Improvement of joint function should be seen within one to two weeks after Hyvisc Injection.

As with any intra-articular injection, a mild inflammatory response (tenderness, heat and swelling) may be seen in the joint following the Hyvisc Injection. This response is self-limiting, but may last from two to five days after treatment.

If inflammation is excessive or severe, the possibility of infection should be considered and appropriate antibiotic therapy instituted.

Contraindications:

There are no known contraindications to the use of Hyvisc (hyaluronate sodium) Injection.

Warnings:

Do not use in horses intended for human consumption. Hyvisc (hyaluronate sodium) Injection must not be administered intravascularly.

Precautions:

Used or partially used syringes should be crushed and disposed of in an appropriate landfill.

Do not use if numerous small air bubbles are present throughout the solution.

Adverse Reactions:

In the clinical trial with Hyvisc (hyaluronate sodium) Injection, a mild, transient post-injection inflammatory response in the joint was reported in 12% of the cases treated. There were no other side effects.

Contact Information:

To report suspected adverse drug experience or for technical service questions, contact Boehringer Ingelheim Animal Health USA Inc. at 1-888-637-4251. For additional information about reporting adverse drug experiences for animal drugs, contact FDA at 1-888-FDA-VETS (1-888-332-8387) or www.fda.gov/reportanimalae.

Safety Margin in Horses:

In toxicity studies of Hyvisc (hyaluronate sodium) Injection in horses, intra-articular doses at one, three, and five times the recommended dose once weekly for three consecutive weeks did not result in any drug related local or systemic toxic effects. The mild, transient post-injection inflammatory response observed within the joints of some horses was qualitatively and quantitatively similar to that detected in the physiologic saline injected controls. In a reproductive study in mares, 16 mL of Hyvisc (10 mg/mL) injected intramuscularly or subcutaneously once or twice during the second or third stage of pregnancy resulted in no adverse effects on the mares or newborn foals.

Storage:

Store under refrigerated conditions, 2° - 8°C (36° - 46°F). Protect from freezing and avoid excessive heat.

How Supplied:

Hyvisc (hyaluronate sodium) Injection, 11 mg/mL, is available in 2 mL prefilled, disposable syringes individually packaged.

References:

1. Radin, E.L. et al: Annals of the Rheumatic Diseases, 30: 322-325, (1971).
2. Swann, D.A. et al: Annals of the Rheumatic Diseases, 33: 318-326, (1974).
3. Hardingham, T.E. and H. Muir: Biochemical et Biophysica Acta, 279: 401-405, (1972).
4. Hascall, V.C. and D. Heingard: Journal of Biological Chemistry, 249: 423-433, (1974).
5. Brandt, K.D. et al: Arthritis and Rheumatism, 19: 1308-1314, (1976).

Approved by FDA under NADA #122-578

Hyvisc® is a registered trademark of Anika Therapeutics, Inc.

Manufactured by:

Anika Therapeutics, Inc.
Bedford, MA 01730 U.S.A.

Distributed by:

Boehringer Ingelheim Animal Health USA Inc.
Duluth, GA 30096

413003-07 AML 520-202/D

Revised 03/2021 © Anika Therapeutics, Inc. 2021

Principal Display Panel – 2 mL display carton

Hyvisc®

(hyaluronate sodium)

Sterile Injection, 11 mg/mL

For intra-articular injection in horses only

Caution: Federal law restricts this drug to use by or on the order of a licensed veterinarian.

Net Contents: 2 mL

Approved by FDA under NADA # 122-578